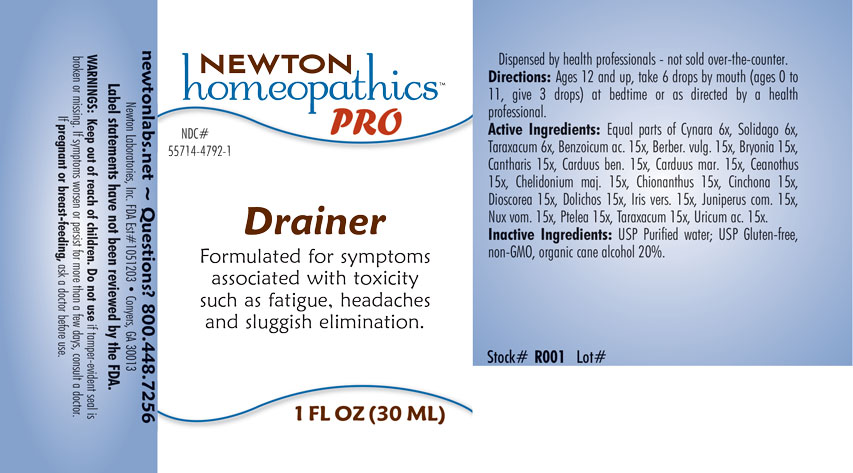 DRUG LABEL: Drainer
NDC: 55714-4792 | Form: LIQUID
Manufacturer: Newton Laboratories, Inc.
Category: homeopathic | Type: HUMAN OTC DRUG LABEL
Date: 20251126

ACTIVE INGREDIENTS: CYNARA SCOLYMUS LEAF 6 [hp_X]/1 mL; BENZOIC ACID 15 [hp_X]/1 mL; BERBERIS VULGARIS ROOT BARK 15 [hp_X]/1 mL; BRYONIA ALBA ROOT 15 [hp_X]/1 mL; LYTTA VESICATORIA 15 [hp_X]/1 mL; CENTAUREA BENEDICTA 15 [hp_X]/1 mL; MILK THISTLE 15 [hp_X]/1 mL; CEANOTHUS AMERICANUS LEAF 15 [hp_X]/1 mL; CHELIDONIUM MAJUS 15 [hp_X]/1 mL; CINCHONA OFFICINALIS BARK 15 [hp_X]/1 mL; DIOSCOREA VILLOSA TUBER 15 [hp_X]/1 mL; CHIONANTHUS VIRGINICUS BARK 15 [hp_X]/1 mL; MUCUNA PRURIENS FRUIT TRICHOME 15 [hp_X]/1 mL; IRIS VERSICOLOR ROOT 15 [hp_X]/1 mL; JUNIPER BERRY 15 [hp_X]/1 mL; STRYCHNOS NUX-VOMICA SEED 15 [hp_X]/1 mL; PTELEA TRIFOLIATA BARK 15 [hp_X]/1 mL; TARAXACUM OFFICINALE 15 [hp_X]/1 mL; URIC ACID 15 [hp_X]/1 mL; SOLIDAGO VIRGAUREA FLOWERING TOP 6 [hp_X]/1 mL
INACTIVE INGREDIENTS: WATER; ALCOHOL

Drainer 4792L

INDICATIONS & USAGE SECTION

Formulated for symptoms associated with toxicity such as fatigue, headaches and sluggish elimination..

DOSAGE & ADMINISTRATION SECTION

Directions: Ages 12 and up, take 6 drops by mouth (ages 0 to 11, give 3 drops) at bedtime or as directed by a health professional.

OTC - ACTIVE INGREDIENT SECTION

Equal parts of Cynara scolymus 6x, Solidago virgaurea 6x, Taraxacum officinale 6x, Benzoicum acidum 15x, Berberis vulgaris 15x, Bryonia 15x, Cantharis 15x, Carduus benedictus 15x, Carduus marianus 15x, Ceanothus americanus 15x, Chelidonium majus 15x, Chionanthus virginica 15x, Cinchona officinalis 15x, Dioscorea villosa 15x, Dolichos pruriens 15x, Iris versicolor 15x, Juniperus communis 15x, Nux vomica 15x, Ptelea trifoliata 15x, Taraxacum officinale 15x, Uricum acidum 15x.

OTC - PURPOSE SECTION

Formulated for symptoms associated with toxicity such as fatigue, headaches and sluggish elimination.

INACTIVE INGREDIENT SECTION

Inactive Ingredients: USP Purified Water; USP Gluten-free, non-GMO, organic cane alcohol 20%.

QUESTIONS SECTION

newtonlabs.net - Questions? 800.448.7256

Newton Laboratories, Inc. FDA Est # 1051203 Conyers, GA 30013

WARNINGS SECTION

WARNINGS: Keep out of reach of children. Do not use if tamper-evident seal is broken or missing. If symptoms worsen or persist for more than a few days, consult a doctor. If pregnant or breast-feeding, ask a doctor before use.

OTC - PREGNANCY OR BREAST FEEDING SECTION

If pregnant or breast-feeding, ask a doctor before use.

OTC - KEEP OUT OF REACH OF CHILDREN SECTION

Keep out of reach of children.